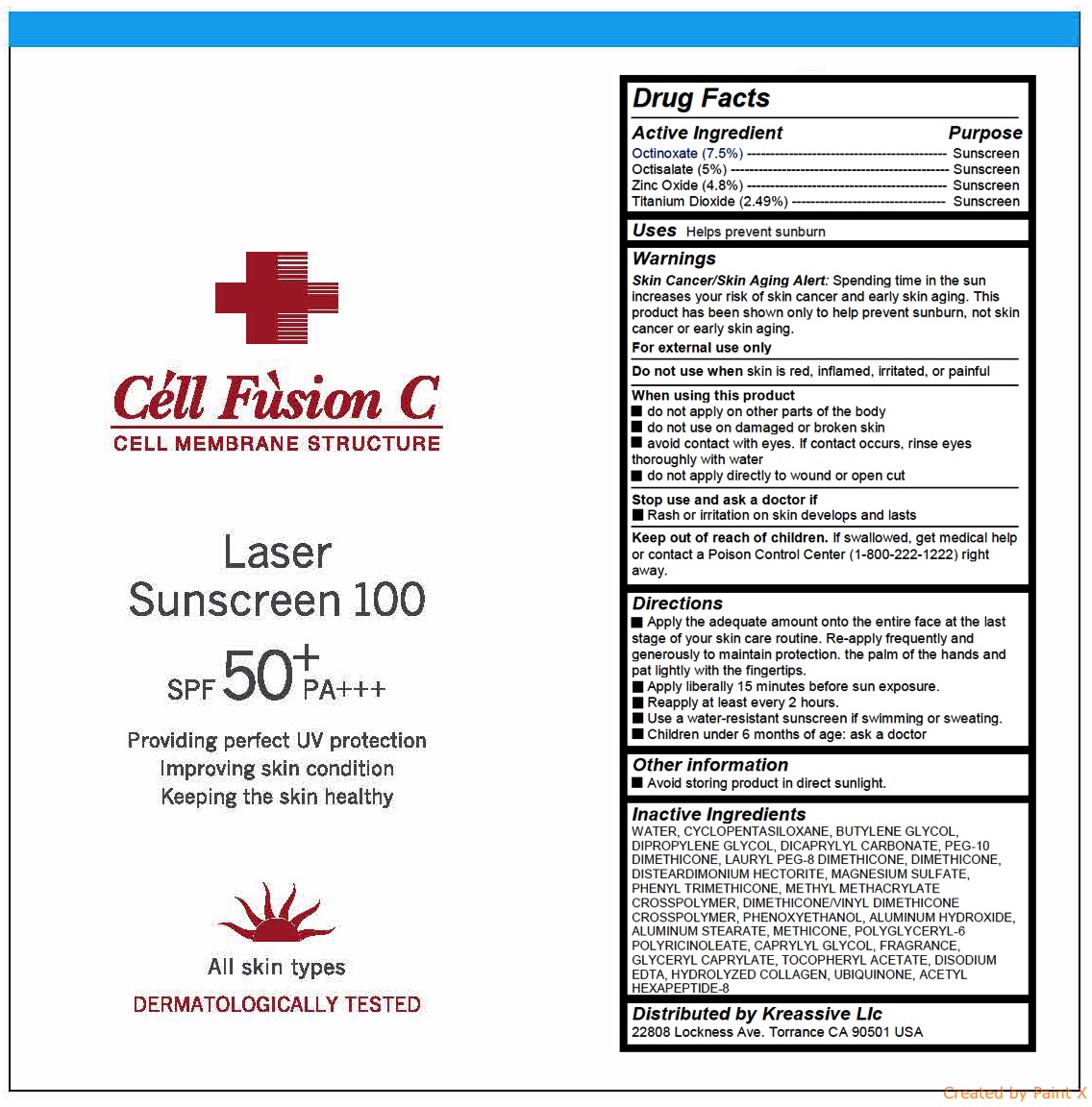 DRUG LABEL: Laser Sunscreen 100
NDC: 52554-1115 | Form: CREAM
Manufacturer: CMS LAB Inc.
Category: otc | Type: HUMAN OTC DRUG LABEL
Date: 20180129

ACTIVE INGREDIENTS: OCTISALATE 1.75 g/35 mL; ZINC OXIDE 1.68 g/35 mL; TITANIUM DIOXIDE 0.8715 g/35 mL; OCTINOXATE 2.625 g/35 mL
INACTIVE INGREDIENTS: WATER; CYCLOMETHICONE 5; BUTYLENE GLYCOL; DISTEARDIMONIUM HECTORITE; DIPROPYLENE GLYCOL; DICAPRYLYL CARBONATE; PEG-10 DIMETHICONE (600 CST); DIMETHICONE

Laser Sunscreen 100

Active ingredients

Octinoxate (7.5%)

Octisalate (5%)

Zinc Oxide (4.8%)

Titanium Dioxide (2.49%)

Purpose

Sunscreen

Uses

Helps prevent sunburn

Warnings

Skin Cancer/Skin Aging Alert: Spending time in the sun increases your risk of skin cancer and early skin aging. This product has been shown only to help prevent sunburn, not skin cancer or early skin aging.

For external use only

Do not use when skin is red, inflamed, irritated, or painful

When using this product

- do not apply on other parts of the body

- do not use on damaged or broken skin

- avoid contact with eyes. If contact occurs, rinse eyes thoroughly with water

- do not apply directly to wound or open cut

Stop use and ask a doctor if

- Rash or irritation on skin develops and lasts

Keep out of reach of children

If swallowed, get medical help or contact a Poison Control Center (1-800-222-1222) right away.

Directions

- Apply the adequate amount onto the entire face at the last stage of your skin care routine. Re-apply frequently and generously to maintain protection. the palm of the hands and pat lightly with the fingertips.

- Apply liberally 15 minutes before sun exposure.

- Reapply at least every 2 hours.

- Use a water-resistant sunscreen if swimming or sweating.

- Children under 6 months of age: ask a doctor

Inactive ingredients

WATER, CYCLOPENTASILOXANE, BUTYLENE GLYCOL, DIPROPYLENE GLYCOL, DICAPRYLYL CARBONATE, PEG-10 DIMETHICONE, LAURYL PEG-8 DIMETHICONE, DIMETHICONE, DISTEARDIMONIUM HECTORITE, MAGNESIUM SULFATE, PHENYL TRIMETHICONE, METHYL METHACRYLATE CROSSPOLYMER, DIMETHICONE/VINYL DIMETHICONE CROSSPOLYMER, PHENOXYETHANOL, ALUMINUM HYDROXIDE, ALUMINUM STEARATE, METHICONE, POLYGLYCERYL-6 POLYRICINOLEATE, CAPRYLYL GLYCOL, FRAGRANCE, GLYCERYL CAPRYLATE, TOCOPHERYL ACETATE, DISODIUM EDTA, HYDROLYZED COLLAGEN, UBIQUINONE, ACETYL HEXAPEPTIDE-8